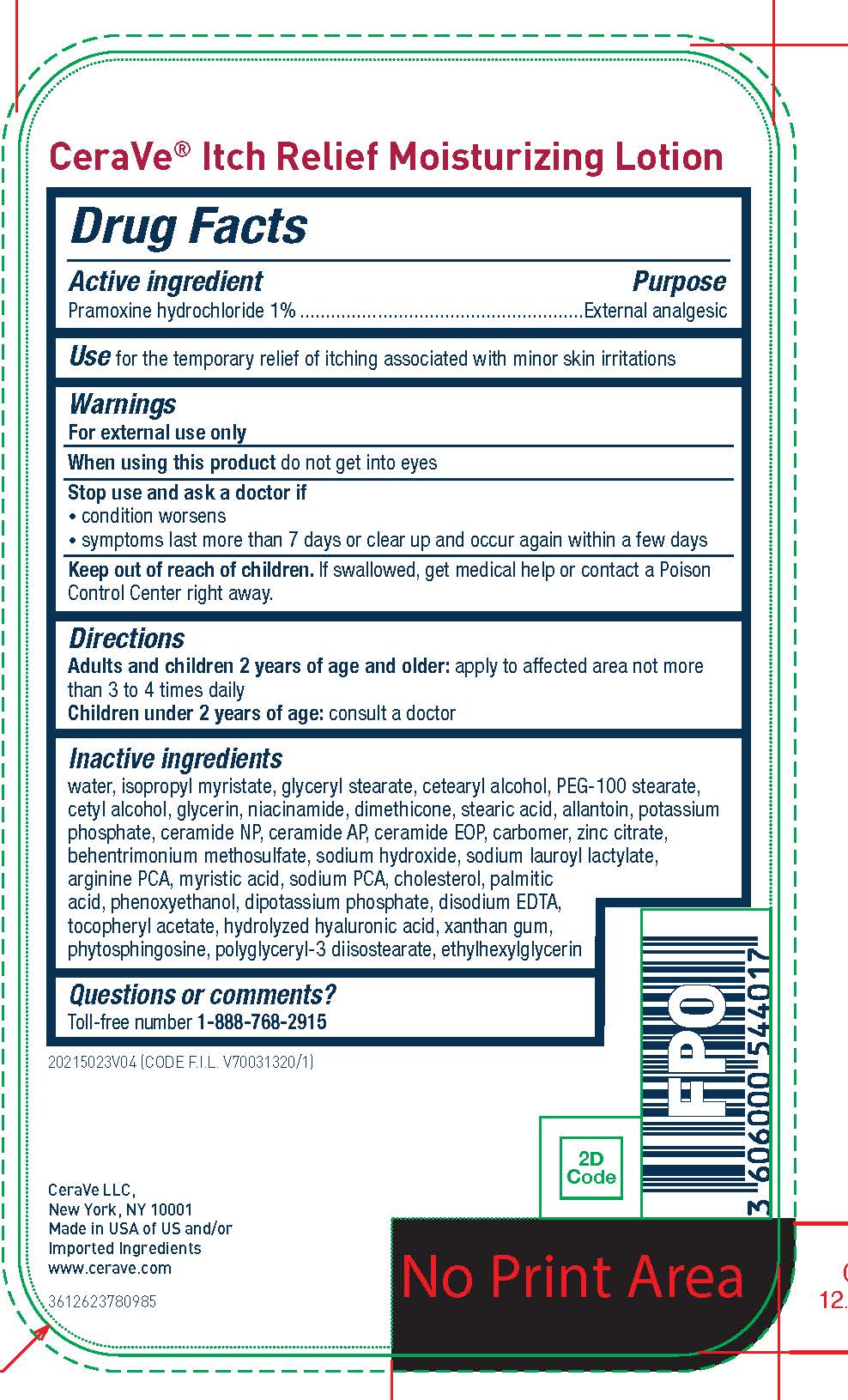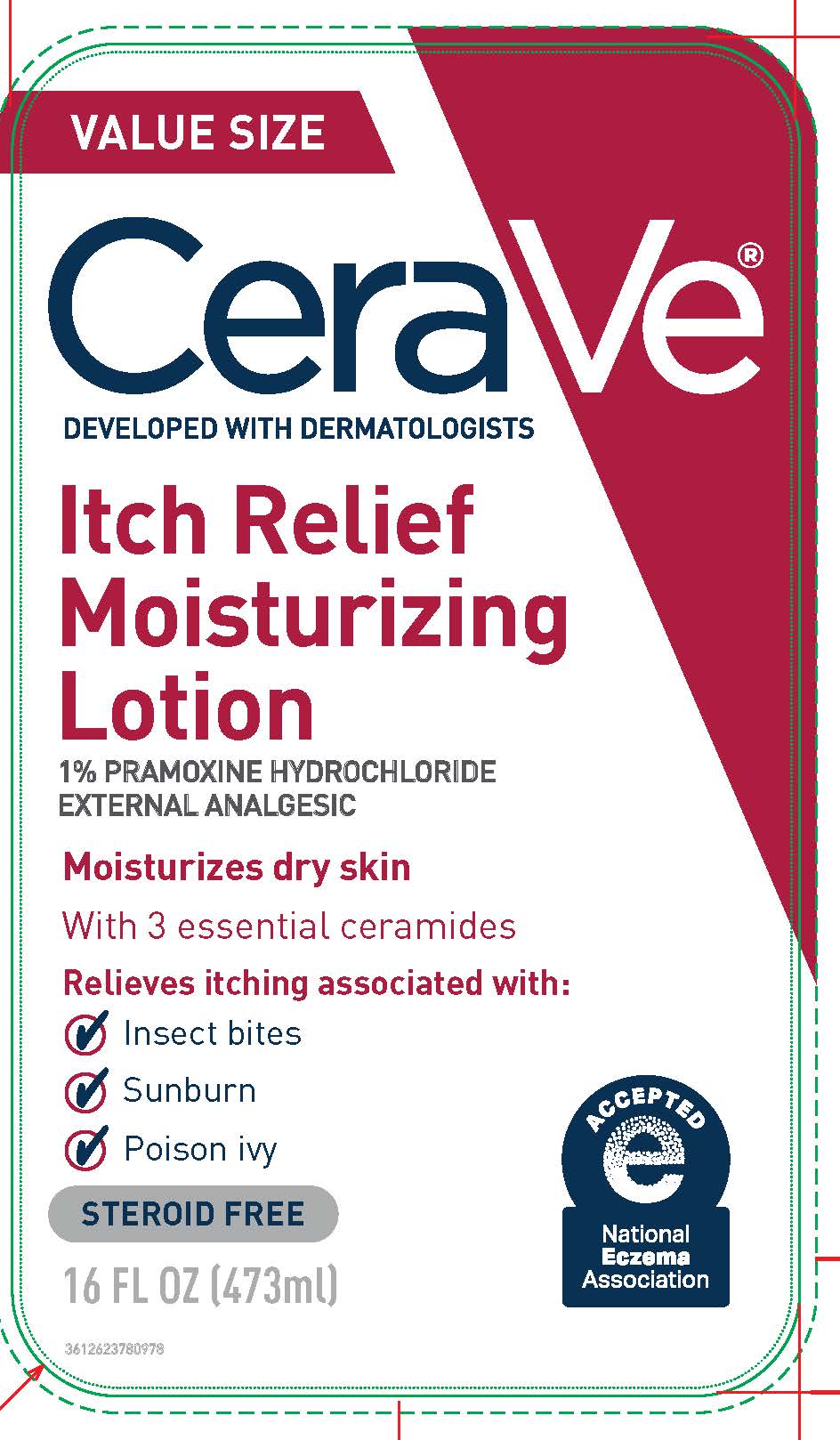 DRUG LABEL: CeraVe Developed with Dermatologists Itch Relief Moisturizing
NDC: 49967-970 | Form: LOTION
Manufacturer: L'Oreal USA Products Inc
Category: otc | Type: HUMAN OTC DRUG LABEL
Date: 20231231

ACTIVE INGREDIENTS: PRAMOXINE HYDROCHLORIDE 1 mg/1 mL
INACTIVE INGREDIENTS: WATER; ISOPROPYL MYRISTATE; CETYL ALCOHOL; STEARIC ACID; CETOSTEARYL ALCOHOL; GLYCERYL MONOSTEARATE; PEG-100 STEARATE; GLYCERIN; DIMETHICONE; NIACINAMIDE; CERAMIDE 3; CERAMIDE 6 II; CERAMIDE 1; PHENOXYETHANOL; XANTHAN GUM; BEHENTRIMONIUM METHOSULFATE; POLYGLYCERYL-3 DIISOSTEARATE; SODIUM HYDROXIDE; ALLANTOIN; ETHYLHEXYLGLYCERIN; SODIUM LAUROYL LACTYLATE; ARGININE PYROGLUTAMATE; EDETATE DISODIUM; POTASSIUM PHOSPHATE, MONOBASIC; POTASSIUM PHOSPHATE, DIBASIC; ZINC CITRATE; SODIUM PYRROLIDONE CARBOXYLATE; PHYTOSPHINGOSINE; CHOLESTEROL; MYRISTIC ACID; PALMITIC ACID; HYALURONIC ACID; CARBOMER HOMOPOLYMER TYPE A (ALLYL PENTAERYTHRITOL CROSSLINKED); .ALPHA.-TOCOPHEROL ACETATE

Drug Facts

Active ingredient

Pramoxine hydrochloride 1%

Purpose

External analgesic

Use

For the temporary relief of itching associated with minor skin irritations

Warnings

For external use only

When using this product

do not get into eyes

Stop use and ask a doctor if

- condition worsens
- symptoms last more than 7 days or clear up and occur again within a few days

Do not use on

- deep or puncture wounds
- animal bites
- serious burns

Keep out of reach of children.

If swallowed, get medical help or contact a Poison Control Center immediately.

Directions

Adults and children 2 years of age and older: apply to affected area not more than 3 to 4 times daily

Children under 2 years of age: consult a doctor

Inactive ingredients

water, isopropyl myristate, PEG-100 stearate, glyceryl stearate, cetearyl alcohol, cetyl alcohol, glycerin, niacinamide, dimethicone, stearic acid, allantoin, potassium phosphate, ceramide NP, ceramide AP, ceramide EOP, carbomer, zinc citrate, behentrimonium methosulfate, sodium hydroxide, sodium lauroyl lactylate, arginine PCA, myristic acid, sodium PCA, cholesterol, palmitic acid, tasmannia lanceolata fruit extract, phenoxyethanol, dipotassium phosphate, disodium EDTA, alcohol denat., tocopheryl acetate, hydrolyzed hyaluronic acid, xanthan gum, phytosphingosine, polyglyceryl-3 diisostearate, ethylhexylglycerin

Questions?

Toll-Free Number 888-768-2915

www.cerave.com